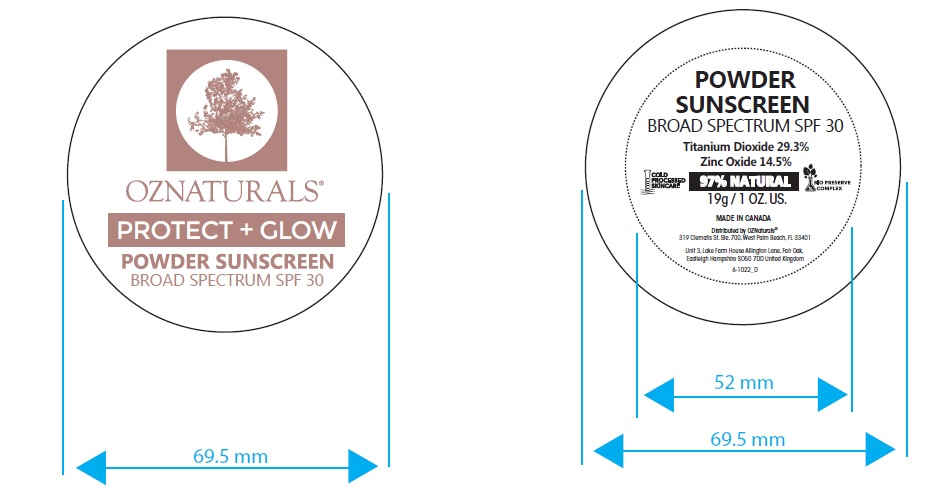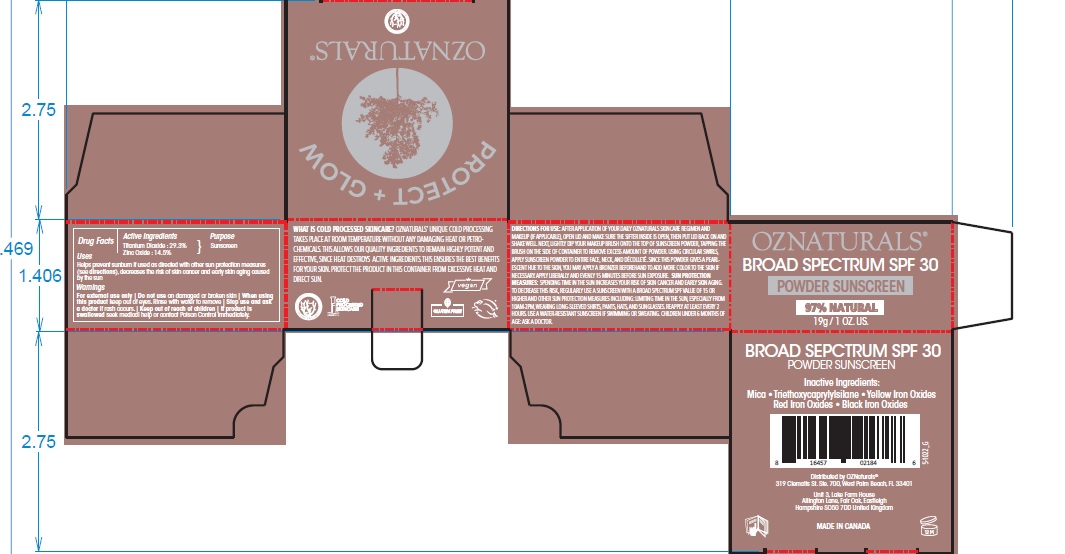 DRUG LABEL: OZNATURALS SUNSCREEN
NDC: 75592-301 | Form: POWDER
Manufacturer: OZ Naturals LLC
Category: otc | Type: HUMAN OTC DRUG LABEL
Date: 20211206

ACTIVE INGREDIENTS: TITANIUM DIOXIDE 293 mg/1 g; ZINC OXIDE 145 mg/1 g
INACTIVE INGREDIENTS: FERROSOFERRIC OXIDE; MICA; FERRIC OXIDE RED; TRIETHOXYCAPRYLYLSILANE; FERRIC OXIDE YELLOW

OZNATURALS POWDER SUNSCREEN

PURPOSE

POWDER SUNSCREEN

BROAD SPECTRUM SPF30

Uses

Helps prevent sunburn if used as directed with other sun protection measures (see directions), decreases the risk of skin cancer and early skin aging caused by the sun.

DIRECTIONS FOR USE:

AFTER APPLICATION OF YOUR DAILY OZNATURALS SKINCARE REGIMEN AND MAKEUP (IF APPLICABLE), OPEN LID AND MAKE SURE THE SIFTER INSIDE IS OPEN, THEN PUT LID BACK ON AND SHAKE WELL. NEXT, LIGHTLY DIP YOUR MAKEUP BRUSH ONTO THE TOP OF SUNSCREEN POWDER, TAPPING THE BRUSH ON THE SIDE OF CONTAINER TO REMOVE EXCESS AMOUNT OF POWDER. USING CIRCULAR SWIRLS, APPLY SUNSCREEN POWDER TO ENTIRE FACE, NECK, AND DÉCOLLETÉ. SINCE THIS POWDER GIVES A PEARLESCENT HUE TO THE SKIN, YOU MAY APPLY A BRONZER BEFOREHAND TO ADD MORE COLOR TO THE SKIN IF NECESSARY.

APPLY LIBERALLY AND EVENLY 15 MINUTES BEFORE SUN EXPOSURE. SUN PROTECTION MEASURES: SPENDING TIME IN THE SUN INCREASES YOUR RISK OF SKIN CANCER AND EARLY SKIN AGING. TO DECREASE THIS RISK, REGULARLY USE A SUNSCREEN WITH A BROAD SPECTRUM SPF VALUE OF 15 OR HIGHER AND OTHER SUN PROTECTION MEASURES INCLUDING: LIMITING TIME IN THE SUN, ESPECIALLY FROM 10AM-2PM, WEARING LONG-SLEEVED SHIRTS, PANTS, HATS, AND SUNGLASSES. REAPPLY AT LEAST EVERY 2 HOURS.

USE A WATER-RESISTANT SUNSCREEN IF SWIMMING OR SWEATING.

CHILDREN UNDER 6 MONTHS OF AGE: ASK A DOCTOR.

ACTIVE INGREDIENT

Titanium Dioxide : 29.3%

Zinc Oxide : 14.5%

PURPOSE: SUNSCREEN

WARNINGS:

For external use only

Do not use on damaged or broken skin

When using this product keep out of eyes.

Rinse with water to remove

Stop use and ask a doctor if rash occurs.

Keep out of reach of children

If product is swallowed seek medical help or contact Poison Control immediately.

Warnings

Keep out of reach of children

INACTIVE INGREDIENTS:

• Mica

• Triethoxycaprylylsilane

• Yellow Iron Oxides

•Red Iron Oxides

• Black Iron Oxides

Distributed by OZNaturals®

319 Clematis St. Ste. 700,
West Palm Beach, FL 33401

Unit 3, Lake Farm House
Allington Lane, Fair Oak, Eastleigh
Hampshire SO50 7DD United Kingdom

MADE IN CANADA

WHAT IS COLD PROCESSED SKINCARE?

OZNATURALS’ UNIQUE COLD PROCESSING TAKES PLACE AT ROOM TEMPERATURE WITHOUT ANY DAMAGING HEAT OR PETROCHEMICALS. THIS ALLOWS OUR QUALITY INGREDIENTS TO REMAIN HIGHLY POTENT AND EFFECTIVE, SINCE HEAT DESTROYS ACTIVE INGREDIENTS. THIS ENSURES THE BEST BENEFITS FOR YOUR SKIN.

PROTECT THE PRODUCT IN THIS CONTAINER FROM EXCESSIVE HEAT AND DIRECT SUN.

Principal Display Panel

OZNATURALS

BROAD SPECTRUM SPF 30

POWDER SUNSCREEN
19g / 1 OZ. US.
97% NATURAL